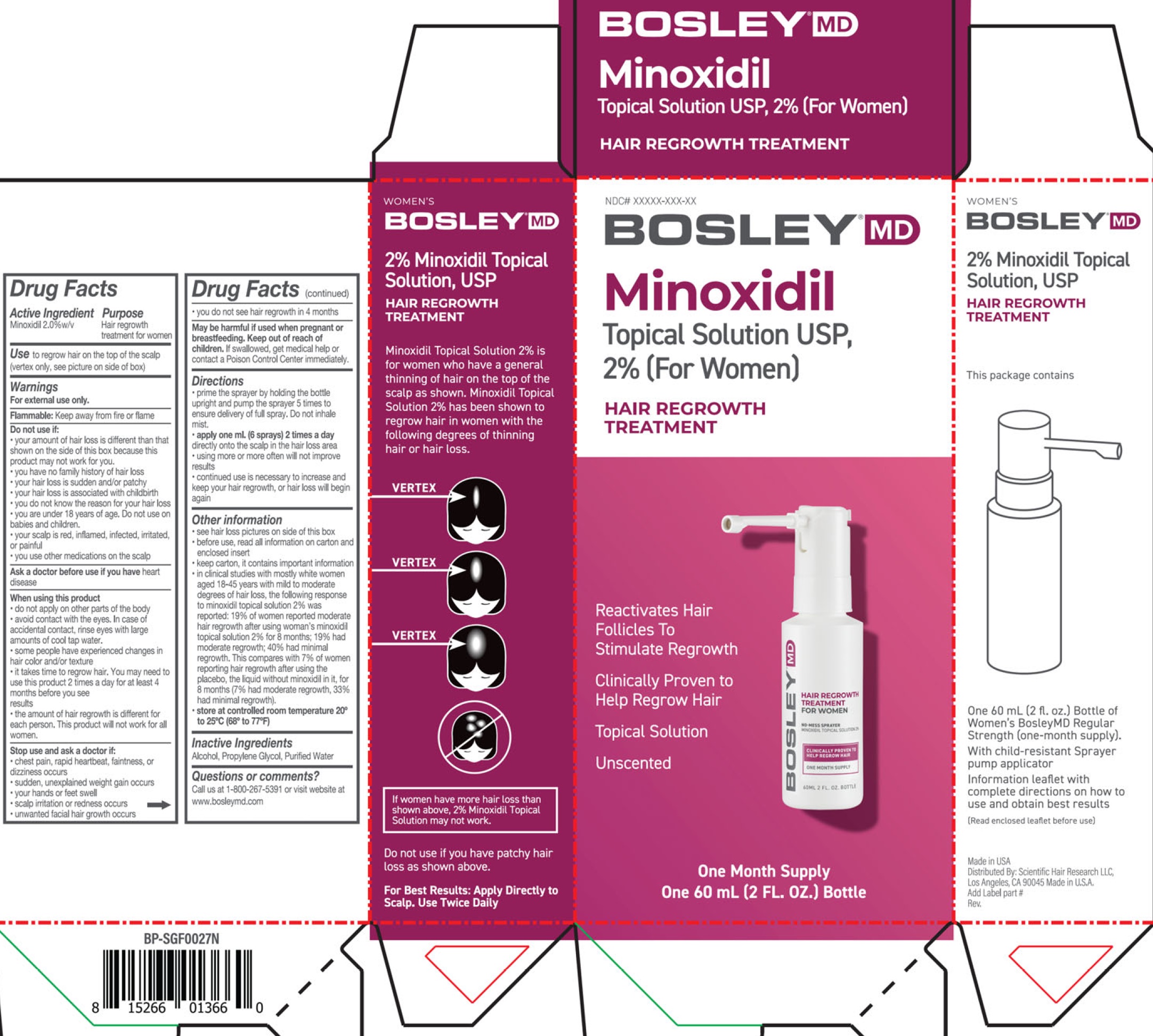 DRUG LABEL: BOSLEY Minoxidil Topical Solution 2 for Women
NDC: 69113-462 | Form: LIQUID
Manufacturer: Scientific Hair Research, LLC
Category: otc | Type: HUMAN OTC DRUG LABEL
Date: 20240221

ACTIVE INGREDIENTS: MINOXIDIL 20 mg/1 mL
INACTIVE INGREDIENTS: ALCOHOL; PROPYLENE GLYCOL; WATER

BOSLEY Minoxidil Topical Solution (2%) for Women

Active Ingredient

Minoxidil 2.0%w/v

Purpose

Hair regrowth treatment for women

Use

to regrow hair on the top of the scalp (vertex only, see picture on side of box)

Warnings

For external use only.

Flammable:keep away from fire or flame

Do not use if:

- your amount of hair loss is different than that shown on the side of this box because this product may not work for you.
- you have no family history of hair loss
- your hair loss is sudden and/or patchy
- your hair loss is associated with childbirth
- you do not know the reason for your hair loss
- you are under 18 years of age. Do not use on babies and children.
- your scalp is red, inflamed, infected, irritated, or painful
- you use other medications on the scalp

Ask a doctor before use if you have

heart disease

When using this product

- do not apply on other parts of the body
- avoid contact with eyes. In case of accidental contact, rinse eyes with large amounts of cool tap water.
- some people have experienced changes in hair color and/or texture
- it takes time to regrow hair. You may need to use this product 2 times a day for at least 4 months before you see results
- the amount of hair regrowth is different for each person. This product will not work for all women.

Stop use and ask a doctor if:

- chest pain, rapid heartbeat, faintness, or dizziness occurs
- sudden, unexplained weight gain occurs
- your hands or feet swell
- scalp irritation or redness occurs
- unwanted facial hair growth occurs
- you do not see hair regrowth in 4 months

May be harmful if used

Keep out of reach of children.

If swallowed, get medical help or contact a Poison Control Center immediately.

Directions

- prime the sprayer by holding the bottle upright and pump the sprayer 5 times to ensure delivery of full spray. Do not inhale mist.
- apply one ml. (6 sprays) 2 times a daydirectly onto the scalp in the hair loss area
- using more or more often will not improve results
- continued use is necessary to increase and keep your hair regrowth, or hair loss will begin again

Other information

- see hair loss pictures on side of this box
- before use, read all information on carton and enclosed insert
- keep carton, it contains important information
- in clinical studies with mostly white women aged 18-45 years with mild to moderate degrees of hair loss, the following response to minoxidil topical solution 2% was reported: 19% of women reported moderate hair regrowth after using woman's minoxidil topical solution 2% for 8 months; 19% had moderate regrowth; 40% had minimal regrowth. This compares with 7% of women reporting hair regrowth after using the placebo, the liquid without minoxidil in it, for 8 months (7% had moderate regrowth, 33% had minimal regrowth).
- store at controlled room temperature 20° to 25°C (68° to 77°F)

Inactive Ingredients

Alcohol, Propylene Glycol, Purified Water

Questions or comments?

Call us at 1-800-267-5391 or visit website at www.bosleymd.com